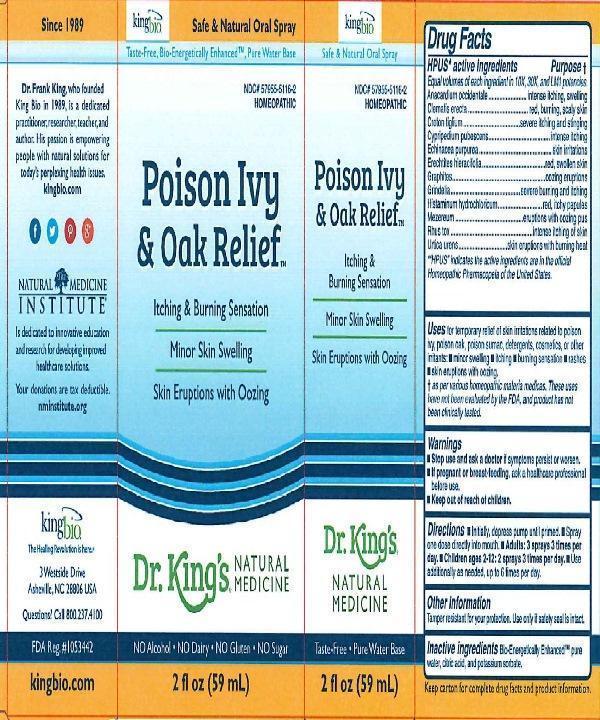 DRUG LABEL: Poison Ivy and Oak Relief
NDC: 57955-5116 | Form: LIQUID
Manufacturer: King Bio Inc.
Category: homeopathic | Type: HUMAN OTC DRUG LABEL
Date: 20160324

ACTIVE INGREDIENTS: ANACARDIUM OCCIDENTALE FRUIT 10 [hp_X]/59 mL; CLEMATIS RECTA FLOWERING TOP 10 [hp_X]/59 mL; CROTON TIGLIUM SEED 10 [hp_X]/59 mL; CYPRIPEDIUM PARVIFOLUM ROOT 10 [hp_X]/59 mL; ECHINACEA PURPUREA 10 [hp_X]/59 mL; ERECHTITES HIERACIIFOLIUS 10 [hp_X]/59 mL; GRAPHITE 10 [hp_X]/59 mL; GRINDELIA HIRSUTULA WHOLE 10 [hp_X]/59 mL; HISTAMINE DIHYDROCHLORIDE 10 [hp_X]/59 mL; DAPHNE MEZEREUM BARK 10 [hp_X]/59 mL; TOXICODENDRON PUBESCENS LEAF 10 [hp_X]/59 mL; URTICA URENS 10 [hp_X]/59 mL
INACTIVE INGREDIENTS: WATER; ANHYDROUS CITRIC ACID; POTASSIUM SORBATE

Poison Ivy and Oak Relief™

ACTIVE INGREDIENT

Drug Facts__________________________________________________________________________________________________________

HPUS active ingredients: Anacardium occidentale, Clematis erecta, Croton tiglium, Cypripedium pubescens, Echinacea purpurea, Erechtites hieracifolia, Graphites, Grindelia, Histaminum hydrochloricum, Mezereum, Rhus toxicodendron, Urtica urens. Equal volumes of each ingredient in 10X, 30X, LM1 potencies.

INDICATIONS AND USAGE

Uses for temporary relief of skin irritations related to poison ivy, poison oak, poison sumac, detergents, cosmetics, or other irritants: •minor swelling •itching •burning sensation •rashes •skin eruptions with oozing.

† as per various homeopathic materia medicas. These uses have not been evaluated by the FDA, and product has not been clinically tested.

Inactive Ingredients:

Bio-Energetically Enhanced™ pure water, citric acid and potassium sorbate.

Warnings

- Stop use and ask a doctor if symptoms persist or worsen.
- If pregnant or breast-feeding, ask a healthcare professional before use.

- Keep out of reach of children.

Directions

- Initially, depress pump until primed.
- Spray one dose directly into mouth.
- Adults: 3 sprays 3 times per day.
- Children ages 2-12: 2 sprays 3 times per day.
- Use additionally as needed, up to 6 times per day.

OTHER SAFETY INFORMATION

Tamper resistant for your protection. Use only if seal is intact. Keep carton for complete drug facts and product information.

PURPOSE

Drug Facts__________________________________________________________________________________________________________

HPUS active ingredients Purpose †

Equal volumes of each ingredient in 10X, 30X, LM1 potencies.

Anacardium occidentale...............................intense itching, swelling

Clematis erecta...........................................red, burning, scaly skin

Croton tiglium........................................severe itching and stinging

Cypripedium pubescens............................................intense itching

Echinacea purpurea..................................................skin irritations

Erechtites hieracifolia............................................red, swollen skin

Graphites.............................................................oozing eruptions

Grindelia................................................severe burning and itching

Histaminum hydrochloricum..................................red, itchy papules

Mezereum.................................................eruption with oozing pus

Rhus toxicodendron........................................intense itching of skin

Urtica urens....................................skin eruptions with burning heat

HPUS indicates the active ingredients are in the official Homeopathic Pharmacopeia of the United States.